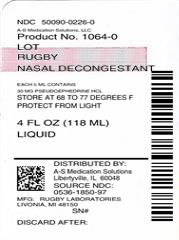 DRUG LABEL: Rugby 
NDC: 50090-0226 | Form: LIQUID
Manufacturer: A-S Medication Solutions
Category: otc | Type: HUMAN OTC DRUG LABEL
Date: 20171221

ACTIVE INGREDIENTS: PSEUDOEPHEDRINE HYDROCHLORIDE 30 mg/5 mL
INACTIVE INGREDIENTS: Sorbitol; Anhydrous Citric Acid; Methylparaben; FD&C Red no. 40; Glycerin; Raspberry; Water; Sodium Benzoate; Saccharin Sodium

Nasal Decongestant liquid

Drug Facts

Active ingredient (in each teaspoonful)

Pseudoephedrine HCl 30 mg

Purpose

Nasal decongestant

Uses

temporarily relieves nasal congestion due to

- common cold
- hay fever or other respiratory allergies

Warnings

Do not exceed recommended dosage.

Stop use and ask a doctor if

- you get nervous, dizzy or sleepless
- symptoms do not get better within 7 days or occur with fever

Ask a doctor before use if you have

- diabetes
- heart disease
- high blood pressure
- thyroid disease
- trouble urinating due to an enlarged prostate gland

Do not use if you are taking a prescription monoamine oxidase inhibitor (MAOI) (certain drugs for depression, psychiatric or emotional conditions, or Parkison's disease), or for 2 weeks after stopping the MAOI drug. If you do not know if your prescription drug contains an MAOI, ask a doctor or pharmacist before taking this product.

PREGNANCY OR BREAST FEEDING

If pregnant or breast-feeding, ask a health professional before use.

Keep out of reach of children. In case of overdose, get medical help or contact a Poison Control Center right away.

Directions

- take every 4 - 6 hours
- do not take more than 4 doses in 24 hours
- use enclosed dosage cup only. Do not use any other device.

adults & children 12 years & over | 2 teaspoonfuls
children 6 to under 12 years | 1 teaspoonful
children under 6 years | do not use

Other information

- store at 20°-25°C (68°-77°F).
- protect from light

Inactive ingredients

artificial raspberry flavor, citric acid, FD&C red #40, glycerin, methylparaben, purified water, saccharin sodium, sodium benzoate, sorbitol solution

Questions or comments?

1-800-645-2158

Distributed by: Rugby Laboratories
17177 N Laurel Park Drive, Suite 233,
Livonia, MI, 48152

HOW SUPPLIED

Product: 50090-0226

NDC: 50090-0226-0 118 mL in a BOTTLE